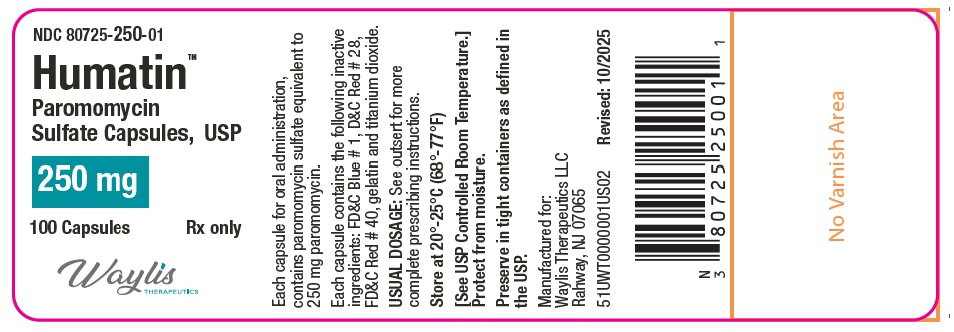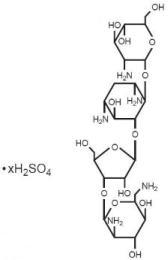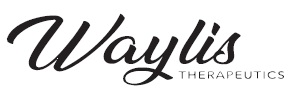 DRUG LABEL: Humatin
NDC: 80725-250 | Form: CAPSULE
Manufacturer: Waylis Therapeutics LLC
Category: prescription | Type: HUMAN PRESCRIPTION DRUG LABEL
Date: 20251113

ACTIVE INGREDIENTS: PAROMOMYCIN SULFATE 250 mg/1 1
INACTIVE INGREDIENTS: FD&C BLUE NO. 1; D&C RED NO. 28; FD&C RED NO. 40; GELATIN; TITANIUM DIOXIDE; D&C YELLOW NO. 10; FD&C BLUE NO. 2; FERROSOFERRIC OXIDE; SHELLAC; PROPYLENE GLYCOL

Rx Only

To reduce the development of drug-resistant bacteria and maintain the effectiveness of HUMATIN™ Capsules, and other antibacterial drugs, HUMATIN™ Capsules should be used only to treat or prevent infections that are proven or strongly suspected to be caused by bacteria.

DESCRIPTION

Paromomycin sulfate is a broad spectrum antibiotic produced by Streptomyces riomosus var. paromomycinus. It is a white, amorphous, stable, water-soluble product. Paromomycin sulfate is designated chemically as 0-2, 6-Diamino-2, 6-dideoxy-β -L-idopyranosyl-(1→3)-0-β -D-ribofuranosyl-(1→5)-0-[2-amino-2-deoxy-α -D-glucopyranosyl-(1→4)]-2-deoxystreptamine sulfate (salt). The molecular formula is C23H45N5O14•xH2SO4, with a molecular weight of 615.64 (base).

Its structural formula is:

Each capsule, for oral administration, contains paromomycin sulfate equivalent to 250 mg paromomycin. Each capsule also contains the following inactive ingredients: FD&C Blue # 1, D&C Red # 28, FD&C Red # 40, gelatin and titanium dioxide. The imprinting ink for the 250 mg capsule contains D&C yellow #10, FD&C blue # 1, FD&C blue # 2, FD&C red # 40, iron oxide black, pharmaceutical shellac glaze, and propylene glycol.

CLINICAL PHARMACOLOGY

The in-vitro and in-vivo antibacterial action of paromomycin closely parallels that of neomycin. It is poorly absorbed after oral administration, with almost 100% of the drug recoverable in the stool.

INDICATIONS AND USAGE

Paromomycin sulfate is indicated for intestinal amebiasis–acute and chronic (NOTE-It is not effective in extraintestinal amebiasis); management of hepatic coma–as adjunctive therapy.

To reduce the development of drug-resistant bacteria and maintain the effectiveness of HUMATIN™ Capsules and other antibacterial drugs, HUMATIN™ Capsules should be used only to treat or prevent infections that are proven or strongly suspected to be caused by susceptible bacteria. When culture and susceptibility information are available, they should be considered in selecting or modifying antibacterial therapy. In the absence of such data, local epidemiology and susceptibility patterns may contribute to the empiric selection of therapy.

CONTRAINDICATIONS

Paromomycin sulfate is contraindicated in individuals with a history of previous hypersensitivity reactions to it. It is also contraindicated in intestinal obstruction.

PRECAUTIONS

Prescribing HUMATIN™ Capsules in the absence of a proven or strongly suspected bacterial infection or a prophylactic indication is unlikely to provide benefit to the patient and increases the risk of the development of drug-resistant bacteria.

The use of this antibiotic, as with other antibiotics, may result in an overgrowth of nonsusceptible organisms, including fungi. Constant observation of the patient is essential. If new infections caused by nonsusceptible organisms appear during therapy, appropriate measures should be taken. The drug should be used with caution in individuals with ulcerative lesions of the bowel to avoid renal toxicity through inadvertent absorption.

Information for Patients

Patients should be counseled that antibacterial drugs including HUMATIN™ Capsules should only be used to treat bacterial infections. They do not treat viral infections (e.g., the common cold). When HUMATIN™ Capsules is prescribed to treat a bacterial infection, patients should be told that although it is common to feel better early in the course of therapy, the medication should be taken exactly as directed. Skipping doses or not completing the full course of therapy may (1) decrease the effectiveness of the immediate treatment and (2) increase the likelihood that bacteria will develop resistance and will not be treatable by HUMATIN™ Capsules or other antibacterial drugs in the future.

PEDIATRIC USE

See DOSAGE AND ADMINISTRATION section.

ADVERSE REACTIONS

Nausea, abdominal cramps, and diarrhea have been reported in patients on doses over 3 g daily.

To report SUSPECTED ADVERSE REACTIONS, Waylis Therapeutics LLC at 844-200-7910 or FDA at 1-800-FDA-1088 or www.fda.gov/medwatch.

DOSAGE AND ADMINISTRATION

Intestinal amebiasis: Adults and Pediatric Patients: Usual dose—25 to 35 mg/kg body weight daily, administered in three doses with meals, for five to ten days.

Management of hepatic coma:

Adults: Usual dose—4 g daily in divided doses, given at regular intervals for five to six days.

HOW SUPPLIED

HUMATIN™ Capsules each contain paromomycin sulfate equivalent to 250 mg paromomycin, are supplied as follows:

NDC 80725-250-01: Bottles of 100

The capsule is Dark Blue Opaque /White Opaque, imprinted with "HP 38" in black ink on the cap and on the body.

STORAGE

Store at 20°-25°C (68°-77°F) [See USP controlled Room Temperature] Protect from moisture.

Preserve in tight containers as defined in the USP.

Call your doctor for medical advice about side effects. You may report side effects to FDA at 1-800-FDA-1088.

MANUFACTURED FOR:

Waylis Therapeutics LLC

Rahway, NJ 07065

51UWT0000002US02

Revised: 10/2025

PACKAGE LABEL.PRINCIPAL DISPLAY PANEL

NDC 80725-250-01

Humatin™

Paromomycin Sulfate Capsules, USP

250 mg

100 Capsules

Rx only